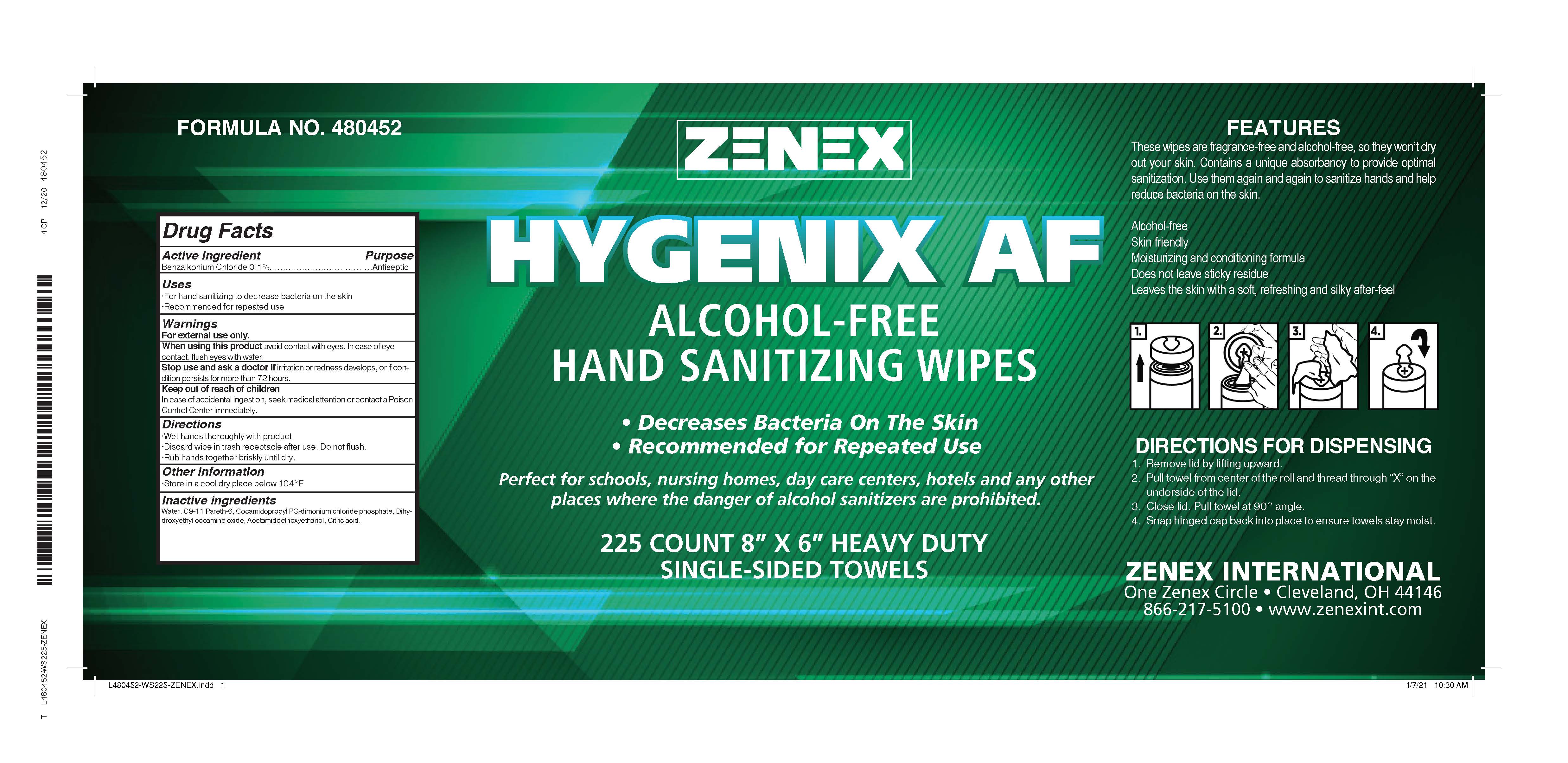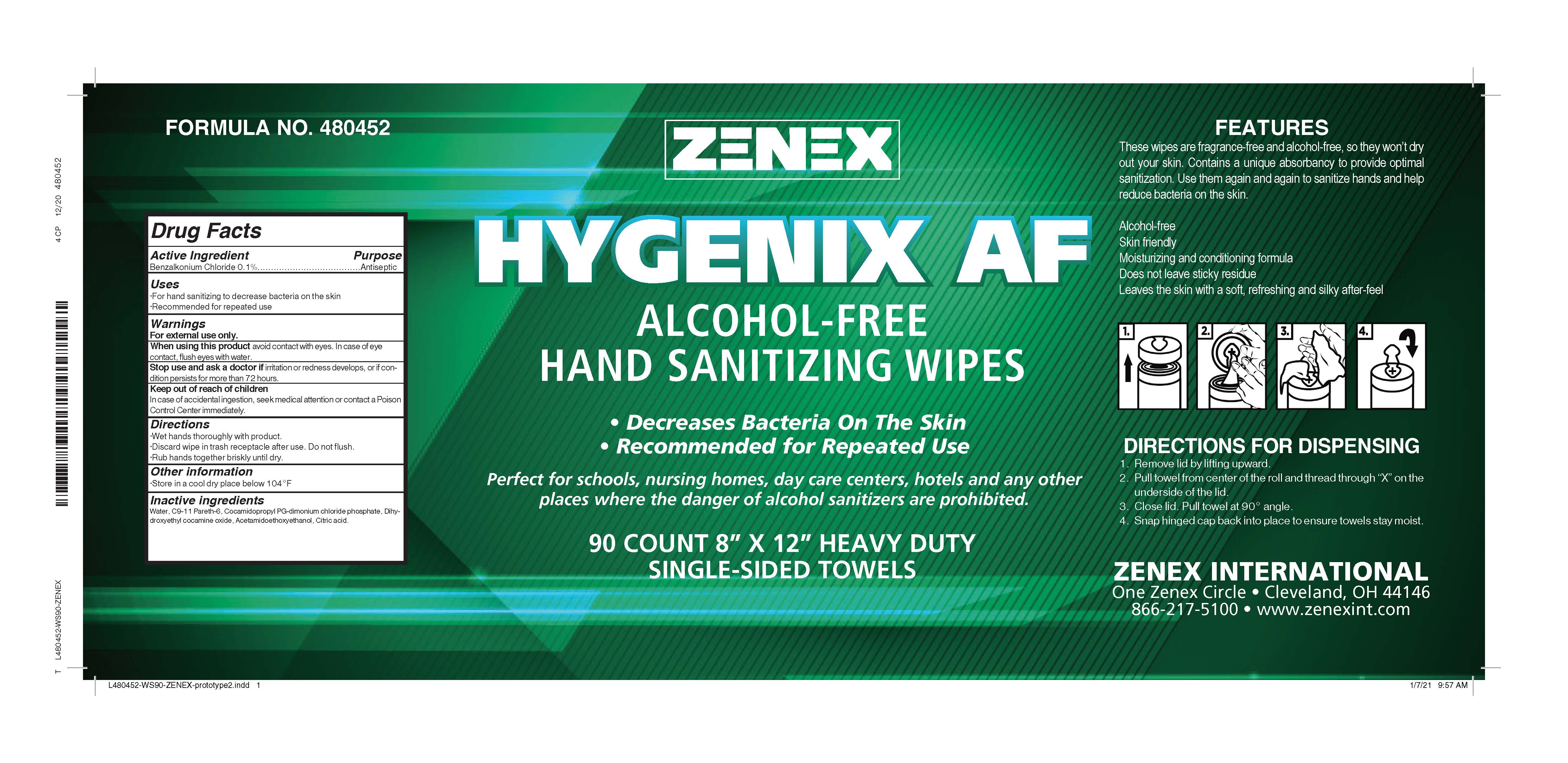 DRUG LABEL: Hygenix AF Wipe
NDC: 74146-243 | Form: CLOTH
Manufacturer: GM Industrial, Inc.
Category: otc | Type: HUMAN OTC DRUG LABEL
Date: 20210617

ACTIVE INGREDIENTS: BENZALKONIUM CHLORIDE 1 mg/1 mL
INACTIVE INGREDIENTS: CITRIC ACID MONOHYDRATE; WATER; COCAMIDOPROPYL PG-DIMONIUM CHLORIDE PHOSPHATE; DIHYDROXYETHYL COCAMINE OXIDE; ACETAMIDOETHOXYETHANOL

Drug Facts

Active Ingredient

Benzalkonium Chloride 0.1

PURPOSE

Antiseptic

INDICATIONS AND USAGE

For hand sanitizing to decrease bacteria on the skin

Recommended for repeated use

WARNINGS

For external use only.

When using this product avoid contact with eyes. In case of eye contact, flush eyes with water.

Stop use and ask a doctor if irritation or redness develops, or if condition persists for more than 72 hours.

Keep out of react of children

In case of accidental ingestion, seek medical attention or contact a Poison Control Center immediately.

Directions

Wet hands thoroughly with product.

Discard wipe in trash receptacle after use. Do not flush.

Rub hands together briskly until dry.

Other information

Store in a cool dry place below 104 °F

INACTIVE INGREDIENT

Water, C9-11 Pareth-6, Cocamidopropyl PG-dimonium chloride phosphate, Dihydroxyethyl cocamine oxide, Acetamidoethoxyethanol, Citric acid.

PACKAGE LABEL

90 CT 74146-243-93

PACKAGE LABEL

74146-243-85